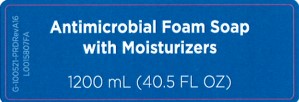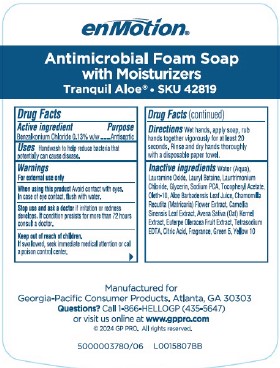 DRUG LABEL: enMotion Antimicrobial

NDC: 54622-700 | Form: SOAP
Manufacturer: Georgia-Pacific Consumer Products LP
Category: otc | Type: HUMAN OTC DRUG LABEL
Date: 20260204

ACTIVE INGREDIENTS: BENZALKONIUM CHLORIDE 1.3 mg/1 mL
INACTIVE INGREDIENTS: WATER; LAURAMINE OXIDE; LAURYL BETAINE; LAURTRIMONIUM CHLORIDE; GLYCERIN; SODIUM PYRROLIDONE CARBOXYLATE; .ALPHA.-TOCOPHEROL ACETATE; OLETH-10; ALOE VERA LEAF; CHAMOMILE; GREEN TEA LEAF; OAT; ACAI; EDETATE SODIUM; CITRIC ACID MONOHYDRATE; D&C GREEN NO. 5; D&C YELLOW NO. 10

enMotion 703.001/703AC
Antimicrobial Foam Soap with Moisturizers-Tranquil Aloe

Claims

enMotion®

Antimicrobial Foam Soap

with Moisturizers

Tranquil Aloe® • SKU 42819

Active ingredient

Benzalkonium chloride 0.13% w/w

Purpose

Antiseptic

Uses

Handwash to help reduce bacteria that potentially can cause disease.

Warnings

For external use only

When using this product

Avoid contact with eyes. In case of eye contact, flush with water.

Stop use and ask a doctor

if irritation or redness develops. If condition persists for more than 72 hours consult a doctor.

Keep out of reach of children.

If swallowed, seek immediate medical attention or call a poison control center.

Directions

Wet hands, apply soap, rub hand together vigorously for at least 20 seconds. Rinse and dry hand thoroughly with a disposable paper towel.

Inactive ingredients

Water (Aqua), Lauramine Oxide, Lauryl Betaine, Laurtrimonium Chloride, Glycerin, Sodium PCA, Tocopheryl Acetate, Oleth-10, Aloe Barbadensis Leaf Juice, Chamomilla Recutita (Matricaria) Flower Extract, Camellia Sinensis Leaf Extract, Avena Sativa (Oat) Kernel Extract, Euterpe Oleracea Fruit Extract, Tetrasodium EDTA, Citric Acid, Fragrance, Green 5, Yellow 10

ADVERSE REACTION

Manufactured for Georgia-Pacific Consumer Products, Atlanta, GA 30303

Questions? Call 1-866-HELLOGP (435-5647)

or visit us online at www.gppro.com

© 2024 GP PRO. All rights reserved.

Principal display panel

Antimicrobial Foam Soap

with Moisturizers

1200 mL (40.5 FL OZ)